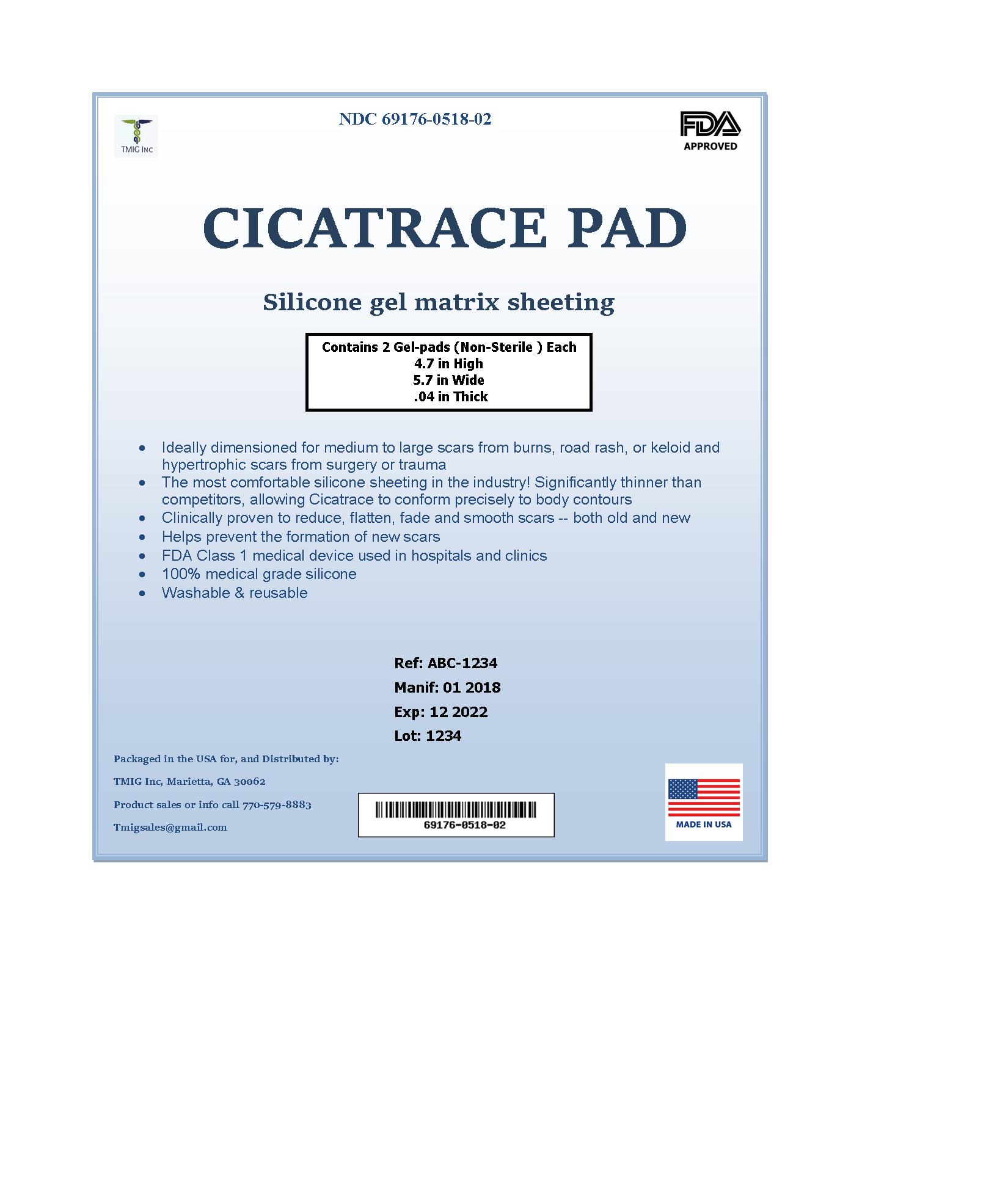 DRUG LABEL: CICATRACE PAD
NDC: 69176-0518 | Form: PATCH
Manufacturer: TMIG Inc
Category: other | Type: MEDICAL DEVICE
Date: 20180614

CICATRACE PAD
(Silicone Gel Matrix)

Rx only

For external use only
Not for ophthalmic use

CICITRACE PAD Description

CICITRACE PAD is intended for non-invasive management of old and new hypertrophic or keloid scars resulting from burns, surgical procedures or trauma wounds.

Each CICITRACE PAD contains: Silicone, Polydimethyl hydrogenmethyl siloxane, Polydimethylsiloxane, and Polydimethylsiloxane hydrogen terminated.

CICITRACE PAD - Clinical Pharmacology

The exact mechanism of silicone gel in improving the appearance of scar tissue remains unknown. However, numerous mechanisms have been suggested to explain the efﬁcacy of silicone gel, including hydration, pressure, temperature, oxygen transmission and silicone absorption. There is some evidence that the treatment affects the stratum corneum and, by reducing evaporation, restores better homeostasis in the tissue. In keloid and hypertrophic scarring, the stratum corneum allows more evaporation of water from the underlying tissue than occurs in normal skin. Silicone pads may prevent this, keeping the stratum corneum in optimal hydration and protecting the skin from environmental hazards, both of which can reduce abnormal scarring. The gel may also affect the stratum corneum by inhibiting mast cell activity, diminishing edema, vasodilatation and excessive extracellular matrix formation but the simple changes in temperature, pressure, oxygen tension and hydration produced by wound coverage probably constitute the main mechanism of action. Another hypothesis is that the effect of static electricity on silicone may inﬂuence the alignment of collagen deposition.

INDICATIONS AND USES

For non-invasive management of old and new hypertrophic or keloid scars resulting from burns, general surgical procedures, injuries or trauma wounds.

Contraindications

CICITRACE PAD is contraindicated in patients with known hypersensitivity to silicone or any of the listed ingredients.

Warnings

For external use only. Avoid contact with eyes, lips or mucous membranes. Do not apply on areas of broken skin. Do not apply on third degree burns and open wounds. Never use on sutured wound until sutures have been removed.

Precautions

Stop use and ask a doctor if irritation develops. In rare instances, silicone sheets may cause a rash on the skin. This condition may result from improper cleansing of the scar area where the silicone pad has been applied. If this product is applied properly and skin irritation still occurs, discontinue use and consult your physician. If ingested, get medical help or contact Poison Control Center right away. KEEP THIS AND ALL MEDICATION OUT OF THE REACH OF CHILDREN.

This medication should be used as directed by your physician during pregnancy or while breast-feeding. Consult your doctor about the risks and benefits.

Adverse Reactions

Rarely the Pads may cause transient redness stinging, burning or irritation and normally disappear on discontinuing the medication.

CICITRACE PAD - Dosage and Administration

1-Wash your hands and the scar area with soap and water. Dry thoroughly.

2-Cut the CICITRACE Pad to fit the scar area so that the edges of the gel pad extend at least 1/4 inch beyond the scar on all sides.

3-Peel of the strip and place the sticky side of the pad directly onto the scar. Leave on for 8-12 hours per day then remove. Do not discard the mylar release strip.

4-When not wearing the pad, place the gel pad (sticky side) back onto the mylar release strip.

5-Discard the pad and replace with a new one every 7 days.

How is CICITRACE PAD Supplied

CICITRACE PAD (Silicone Gel Matrix) is supplied in:
TWO (2) Large Non-Sterile Silicone Gel Pads – 4.7" × 5.7" in 1 Carton | 69176-0518-02

STORAGE AND HANDLING

Store at 20°-25°C (68° to 77°F); Keep away from heat and protect from freezing. [See USP Controlled Room Temperature.]

PRINCIPAL DISPLAY PANEL - 2 Pad Pouch Carton

TMIG Inc.

NDC 69176-0518-02

CICITRACE PAD

TWO (2) Gel Pad - 4.7' x 5.7'' (Non - Sterile)

SILICONE GEL MATRIX

RX ONLY